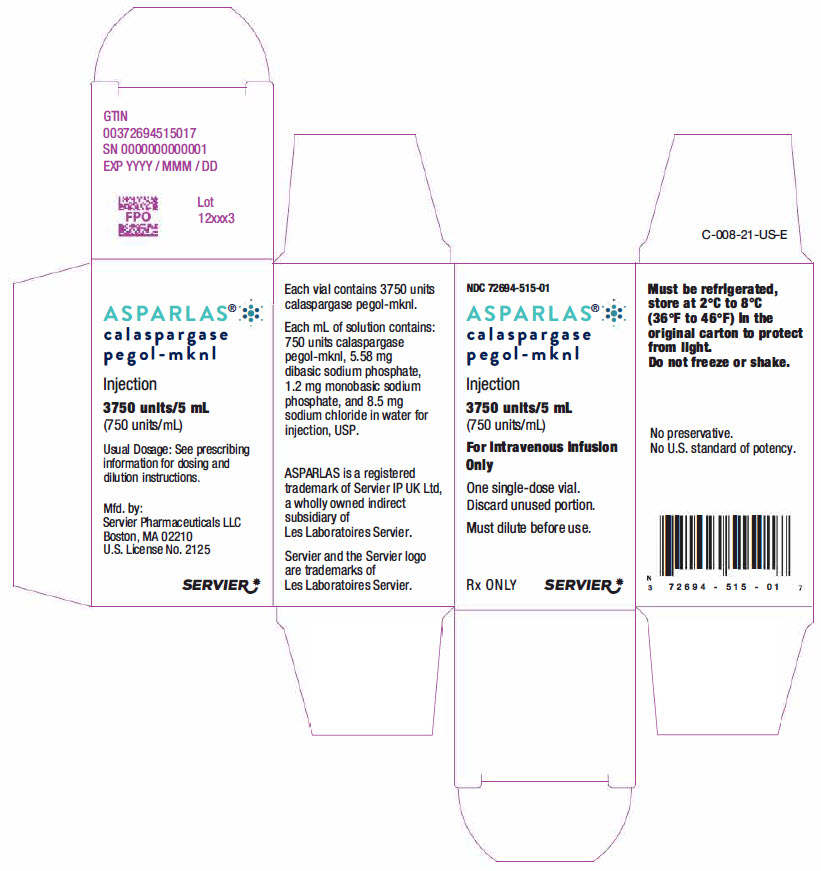 DRUG LABEL: asparlas
NDC: 72694-515 | Form: INJECTION, SOLUTION
Manufacturer: Servier Pharmaceuticals LLC
Category: prescription | Type: HUMAN PRESCRIPTION DRUG LABEL
Date: 20241008

ACTIVE INGREDIENTS: CALASPARGASE PEGOL 750 U/1 mL
INACTIVE INGREDIENTS: SODIUM PHOSPHATE, MONOBASIC, DIHYDRATE; SODIUM PHOSPHATE, DIBASIC, UNSPECIFIED FORM; SODIUM CHLORIDE; WATER

HIGHLIGHTS OF PRESCRIBING INFORMATION

These highlights do not include all the information needed to use ASPARLAS safely and effectively. See full prescribing information for ASPARLAS.
ASPARLAS® (calaspargase pegol-mknl) injection, for intravenous use
Initial U.S. Approval: 2018

RECENT MAJOR CHANGES

Warnings and Precautions: Hepatotoxicity (5.5) | 11/2023

1 INDICATIONS AND USAGE

ASPARLAS is an asparagine specific enzyme indicated as a component of a multi-agent chemotherapeutic regimen for the treatment of acute lymphoblastic leukemia in pediatric and young adult patients age 1 month to 21 years. (1.1)

2 DOSAGE AND ADMINISTRATION

- Recommended Dosage: 2,500 units/m^2 intravenously no more frequently than every 21 days. (2.1)
- See Full Prescribing Information for important details regarding dosing modifications and preparation and administration. (2.2, 2.3, 2.4)

3 DOSAGE FORMS AND STRENGTHS

Injection: 3,750 units/5 mL (750 units/mL) in a single-dose vial. (3)

4 CONTRAINDICATIONS

- History of serious hypersensitivity reactions to pegylated L-asparaginase. (4)
- History of serious thrombosis during L-asparaginase therapy. (4)
- History of serious pancreatitis related to previous L-asparaginase treatment. (4)
- History of serious hemorrhagic events during previous L-asparaginase therapy. (4)
- Severe hepatic impairment. (4)

5 WARNINGS AND PRECAUTIONS

- Hypersensitivity: Observe patients for one hour after administration. Discontinue ASPARLAS in patients with serious hypersensitivity reactions. (5.1)
- Pancreatitis: Discontinue ASPARLAS in patients with pancreatitis. Monitor blood glucose. (5.2)
- Thrombosis: Discontinue ASPARLAS for severe or life-threatening thrombosis. (5.3)
- Hemorrhage: Discontinue ASPARLAS for severe or life-threatening hemorrhage. Evaluate for etiology and treat. (5.4)
- Hepatotoxicity, including hepatic veno-occlusive disease (VOD): Monitor for toxicity through recovery from cycle. Discontinue ASPARLAS for severe liver toxicity. (5.5)

6 ADVERSE REACTIONS

The most common (incidence ≥10%) grade ≥3 adverse reactions were elevated transaminase, bilirubin increased, pancreatitis, and abnormal clotting studies. (6.1)

To report SUSPECTED ADVERSE REACTIONS, contact Servier Pharmaceuticals LLC at 1-800-807-6124 or FDA at 1-800-FDA-1088 or www.fda.gov/medwatch.

8 USE IN SPECIFIC POPULATIONS

Lactation: Advise not to breastfeed. (8.2)

FULL PRESCRIBING INFORMATION

1 INDICATIONS AND USAGE

1.1 Acute Lymphoblastic Leukemia

ASPARLAS is indicated as a component of a multi-agent chemotherapeutic regimen for the treatment of acute lymphoblastic leukemia in pediatric and young adult patients age 1 month to 21 years.

2 DOSAGE AND ADMINISTRATION

2.1 Recommended Dosage

The recommended dose of ASPARLAS is 2,500 units/m^2 given intravenously no more frequently than every 21 days.

2.2 Recommended Premedication

Premedicate patients with acetaminophen, an H-1 receptor blocker (such as diphenhydramine), and an H-2 receptor blocker (such as famotidine) 30-60 minutes prior to administration of ASPARLAS to decrease the risk and severity of both infusion and hypersensitivity reactions [see Warnings and Precautions (5.1)].

2.3 Recommended Monitoring and Dosage Modifications for Adverse Reactions

Monitor patients at least weekly with bilirubin, transaminases, glucose, and clinical examinations until recovery from the cycle of therapy. If an adverse reaction should occur, modify treatment according to Table 1.

Table 1: Dosage Modifications
Adverse Reaction | Severity [Grade 1 is mild, grade 2 is moderate, grade 3 is severe, and grade 4 is life-threatening.] | Action
Infusion Reaction/ Hypersensitivity Reaction [see Warnings and Precautions (5.1)] | Grade 1 | - Reduce the infusion rate by 50%
Infusion Reaction/ Hypersensitivity Reaction [see Warnings and Precautions (5.1)] | Grade 2 | - Interrupt the infusion of ASPARLAS - Treat the symptoms - When symptoms resolve, resume the infusion and reduce the infusion rate by 50%
Infusion Reaction/ Hypersensitivity Reaction [see Warnings and Precautions (5.1)] | Grade 3 to 4 | - Discontinue ASPARLAS permanently
Pancreatitis [see Warnings and Precautions (5.2)] | Grades 3 to 4 | - Hold ASPARLAS for elevations in lipase or amylase >3 × upper limit of normal (ULN) until enzyme levels stabilize or are declining - Discontinue ASPARLAS permanently if clinical pancreatitis is confirmed
Thrombosis [see Warnings and Precautions (5.3)] | Uncomplicated deep vein thrombosis | - Hold ASPARLAS - Treat with appropriate antithrombotic therapy - Upon resolution of symptoms consider resuming ASPARLAS, while continuing antithrombotic therapy
Thrombosis [see Warnings and Precautions (5.3)] | Severe or life-threatening thrombosis | - Discontinue ASPARLAS permanently - Treat with appropriate antithrombotic therapy
Hemorrhage [see Warnings and Precautions (5.4)] | Grade 3 to 4 | - Hold ASPARLAS - Evaluate for coagulopathy and consider clotting factor replacement as needed - Resume ASPARLAS with the next scheduled dose if bleeding is controlled
Hepatotoxicity [see Warnings and Precautions (5.5)] | Total bilirubin more than 3 times to no more than 10 times the ULN | - Hold ASPARLAS until total bilirubin is ≤1.5 times the ULN
Hepatotoxicity [see Warnings and Precautions (5.5)] | Total bilirubin more than 10 times the ULN | - Discontinue ASPARLAS and do not make up for missed doses

2.4 Preparation and Administration

ASPARLAS is a clear and colorless solution. Visually inspect parenteral drug products for particulate matter, cloudiness, or discoloration prior to administration. If any of these are present, discard the vial. Do not administer if ASPARLAS has been shaken or vigorously agitated, frozen, or stored at room temperature for more than 48 hours.

- Dilute ASPARLAS in 100 mL of 0.9% Sodium Chloride Injection, USP or 5% Dextrose Injection, USP using sterile/aseptic technique. Discard any unused portion left in a vial.
- After dilution, administer immediately into a running infusion of either 0.9% sodium chloride or 5% dextrose, respectively.
- Administer the dose over a period of 1 hour.
- Do not infuse other drugs through the same intravenous line during administration of ASPARLAS.
- The diluted solution may be stored for up to 4 hours at room temperature (15°C to 25°C [59°F to 77°F]) or refrigerated at 2°C to 8°C (36°F to 46°F) for up to 24 hours.
- Protect from light. Do not shake or freeze.

3 DOSAGE FORMS AND STRENGTHS

Injection: 3,750 units/5 mL (750 units/mL) clear, colorless solution in a single-dose vial.

4 CONTRAINDICATIONS

ASPARLAS is contraindicated in patients with:

- History of serious hypersensitivity reactions, including anaphylaxis, to pegylated L-asparaginase therapy [see Warnings and Precautions (5.1)]
- History of serious pancreatitis during previous L-asparaginase therapy [see Warnings and Precautions (5.2)]
- History of serious thrombosis during previous L-asparaginase therapy [see Warnings and Precautions (5.3)]
- History of serious hemorrhagic events during previous L-asparaginase therapy [see Warnings and Precautions (5.4)]
- Severe hepatic impairment [see Warnings and Precautions (5.5)]

5 WARNINGS AND PRECAUTIONS

5.1 Hypersensitivity

Grade 3 and 4 hypersensitivity reactions, including anaphylaxis, have been reported in clinical trials with ASPARLAS with an incidence between 7 and 21% [see Contraindications (4), Adverse Reactions (6.1)]. Hypersensitivity reactions observed with other asparaginases include angioedema, lip swelling, eye swelling, erythema, blood pressure decreased, bronchospasm, dyspnea, pruritus, and rash [see Adverse Reactions (6.1)].

Premedicate patients 30-60 minutes prior to administration of ASPARLAS [see Dosage and Administration (2.2)]. Because of the risk of serious allergic reactions (e.g., life-threatening anaphylaxis), administer ASPARLAS in a clinical setting with resuscitation equipment and other agents necessary to treat anaphylaxis (e.g., epinephrine, oxygen, intravenous steroids, antihistamines) [see Dosage and Administration (2.4)] and observe patients for 1 hour after administration. Discontinue ASPARLAS in patients with serious hypersensitivity reactions.

5.2 Pancreatitis

Cases of pancreatitis have been reported in clinical trials with ASPARLAS with an incidence between 12 and 16% [see Adverse Reactions (6.1)]. Hemorrhagic or necrotizing pancreatitis have been reported with other asparaginases.

Inform patients of the signs and symptoms of pancreatitis, which, if left untreated, could be fatal. Assess serum amylase and/or lipase levels to identify early signs of pancreatic inflammation. Discontinue ASPARLAS if pancreatitis is suspected; if pancreatitis is confirmed, do not resume ASPARLAS [see Dosage and Administration (2.3)].

5.3 Thrombosis

Serious thrombotic events, including sagittal sinus thrombosis, have been reported in clinical trials with ASPARLAS with an incidence of 9 to 12%. Discontinue ASPARLAS in patients experiencing serious thrombotic events [see Dosage and Administration (2.3), Adverse Reactions (6.1)].

5.4 Hemorrhage

Hemorrhage associated with increased prothrombin time (PT), increased partial thromboplastin time (PTT), and hypofibrinogenemia have been reported in patients receiving ASPARLAS [see Adverse Reactions (6.1)]. Evaluate patients with signs and symptoms of hemorrhage with coagulation parameters including PT, PTT, fibrinogen. Consider appropriate replacement therapy in patients with severe or symptomatic coagulopathy [see Dosage and Administration (2.3)].

5.5 Hepatotoxicity, Including Hepatic Veno-Occlusive Disease

Hepatotoxicity, including severe, life-threatening, and potentially fatal cases of hepatic veno-occlusive disease (VOD), have been observed in patients treated with ASPARLAS in combination with standard chemotherapy, including during the induction phase of multiphase chemotherapy [see Adverse Reactions (6)]. Do not administer ASPARLAS to patients with severe hepatic impairment [see Contraindications (4)].

Evaluate bilirubin and transaminases prior to each dose of ASPARLAS and at least weekly, during cycles of treatment that include ASPARLAS, through 6 weeks after the last dose of ASPARLAS. Monitor frequently for signs and symptoms of hepatic VOD, which may include rapid weight gain, fluid retention with ascites, hepatomegaly (which may be painful), and rapid increase of bilirubin. For patients who develop abnormal liver tests after ASPARLAS, more frequent monitoring for liver test abnormalities and clinical signs and symptoms of VOD is recommended. In the event of serious liver toxicity, including VOD, discontinue treatment with ASPARLAS and provide supportive care [see Dosage and Administration (2.3)].

6 ADVERSE REACTIONS

The following clinically significant adverse reactions are described elsewhere in the labeling:

- Hypersensitivity [see Warnings and Precautions (5.1)]
- Pancreatitis [see Warnings and Precautions (5.2)]
- Thrombosis [see Warnings and Precautions (5.3)]
- Hemorrhage [see Warnings and Precautions (5.4)]
- Hepatotoxicity, including VOD [see Warnings and Precautions (5.5)]

6.1 Clinical Trials Experience

Because clinical trials are conducted under widely varying conditions, adverse reaction rates observed in the clinical trials of a drug cannot be directly compared to rates in the clinical trials of another drug and may not reflect the rates observed in practice.

Study DFCI 11-001

The safety of ASPARLAS was investigated in Study DFCI 11-001, an open-label, randomized, active-controlled multicenter clinical trial that treated 237 children and adolescents with newly diagnosed ALL or lymphoblastic lymphoma, with ASPARLAS 2,500 U/m^2 (n=118) or pegaspargase 2,500 U/m^2 (n=119) as part of a Dana-Farber Cancer Institute (DFCI) ALL Consortium backbone therapy. The median age on enrollment was 5 years (range, 1-20 years). The majority of patients were male (62%) and white (70%). Most patients were considered standard risk (SR, 59%) and had B-cell lineage ALL (87%).

The median number of doses during the study was 11 doses for ASPARLAS (administered every three weeks) and 16 doses for pegaspargase (administered every two weeks). The median duration of exposure was 8 months for both ASPARLAS and pegaspargase.

There was 1 fatal adverse reaction (multi-organ failure in the setting of chronic pancreatitis associated with a pancreatic pseudocyst).

Table 2 summarizes the incidence of selected grades ≥3 adverse reactions that occurred in 2 or more patients receiving ASPARLAS. Because not all grade 1 and 2 adverse reactions were collected prospectively, only grade 3 and 4 adverse events are presented in Table 2.

Table 2: Selected Grades ≥3 Adverse Reactions in Patients Receiving ASPARLAS with Multi-Agent Chemotherapy (Study DFCI 11-001) [ASPARLAS or pegaspargase were administered as a component of multi-agent chemotherapy regimens.]
Adverse Reaction [Grouped terms: Elevated transaminase: Alanine aminotransferase increased, Aspartate aminotransferase increased, Transaminases increased; Bilirubin increased: Bilirubin conjugated increased, Blood bilirubin increased; Pancreatitis: Amylase increased, Lipase increased, Pancreatic necrosis, Pancreatitis, Pancreatitis relapsing; Abnormal clotting studies: Activated partial thromboplastin time prolonged, Blood fibrinogen decreased; Diarrhea: Colitis, Diarrhea, Enterocolitis, Neutropenic colitis; Hypersensitivity: Anaphylactic reaction, Drug hypersensitivity, Hypersensitivity; Embolic and thrombotic events SMQ: Device related thrombosis, Disseminated intravascular coagulation, Embolism, Intracardiac thrombus, Intracranial venous sinus thrombosis, Pulmonary embolism, Superior sagittal sinus thrombosis, Thrombosis in device, Venous thrombosis, Venous thrombosis limb; Sepsis: Bacterial sepsis, Sepsis; Dyspnea: Hypoxia, Respiratory failure; Hemorrhages SMQ (excludes laboratory terms): Disseminated intravascular coagulation, Epistaxis, Hematoma, Hemorrhage intracranial, Melena, Esophageal ulcer hemorrhage, Small intestinal hemorrhage, Upper gastrointestinal hemorrhage; Fungal infection: Fungal infection, Hepatic infection fungal, Respiratory tract infection fungal, Splenic infection fungal, Systemic candida; Pneumonia: Lung infection, Pneumonia, Pneumonitis; Arrhythmia: Atrioventricular block complete, Sinus tachycardia, Ventricular arrhythmia; Cardiac failure: Ejection fraction decreased, Left ventricular dysfunction.] | ASPARLAS 2,500 U/m^2 N=118 | Pegaspargase 2,500 U/m^2 N=119
Adverse Reaction [Grouped terms: Elevated transaminase: Alanine aminotransferase increased, Aspartate aminotransferase increased, Transaminases increased; Bilirubin increased: Bilirubin conjugated increased, Blood bilirubin increased; Pancreatitis: Amylase increased, Lipase increased, Pancreatic necrosis, Pancreatitis, Pancreatitis relapsing; Abnormal clotting studies: Activated partial thromboplastin time prolonged, Blood fibrinogen decreased; Diarrhea: Colitis, Diarrhea, Enterocolitis, Neutropenic colitis; Hypersensitivity: Anaphylactic reaction, Drug hypersensitivity, Hypersensitivity; Embolic and thrombotic events SMQ: Device related thrombosis, Disseminated intravascular coagulation, Embolism, Intracardiac thrombus, Intracranial venous sinus thrombosis, Pulmonary embolism, Superior sagittal sinus thrombosis, Thrombosis in device, Venous thrombosis, Venous thrombosis limb; Sepsis: Bacterial sepsis, Sepsis; Dyspnea: Hypoxia, Respiratory failure; Hemorrhages SMQ (excludes laboratory terms): Disseminated intravascular coagulation, Epistaxis, Hematoma, Hemorrhage intracranial, Melena, Esophageal ulcer hemorrhage, Small intestinal hemorrhage, Upper gastrointestinal hemorrhage; Fungal infection: Fungal infection, Hepatic infection fungal, Respiratory tract infection fungal, Splenic infection fungal, Systemic candida; Pneumonia: Lung infection, Pneumonia, Pneumonitis; Arrhythmia: Atrioventricular block complete, Sinus tachycardia, Ventricular arrhythmia; Cardiac failure: Ejection fraction decreased, Left ventricular dysfunction.] | Grades ≥3 n (%) [Grading is based on the Common Terminology Criteria for Adverse Events (CTCAE) v4.0.] | Grades ≥3 n (%)
Elevated transaminase | 61 (52) | 79 (66)
Bilirubin increased | 24 (20) | 30 (25)
Pancreatitis | 21 (18) | 29 (24)
Abnormal clotting studies | 17 (14) | 25 (21)
Diarrhea | 10 (9) | 6 (5)
Hypersensitivity | 9 (8) | 8 (7)
Embolic and thrombotic events | 9 (8) | 10 (8)
Sepsis | 6 (5) | 7 (6)
Dyspnea | 5 (4) | 1 (1)
Hemorrhages | 5 (4) | 5 (4)
Fungal infection | 4 (3) | 3 (3)
Pneumonia | 4 (3) | 8 (7)
Arrhythmia | 2 (2) | 1 (1)
Cardiac failure | 2 (2) | 1 (1)

In the subgroup of patients with B-cell lineage ALL, the complete remission rate in the ASPARLAS arm was 98% (95/97), compared to 99% in the pegaspargase arm; the Kaplan-Meier estimates of overall survival of the treatment arms were comparable.

Study AALL07P4

The safety of ASPARLAS was also evaluated in Study AALL07P4, an open-label, randomized, active-controlled, multicenter clinical trial that treated patients with newly diagnosed high-risk B-precursor ALL using ASPARLAS 2,500 U/m^2 (n=43) or 2,100 U/m^2 (n=68), or pegaspargase 2,500 U/m^2 (n=52), as a component of an augmented Berlin-Frankfurt-Münster (BFM) therapy regimen. The median age was 11 years (range, 1-26 years); the median duration of exposure was 7 months for both ASPARLAS and pegaspargase. In this study, the induction mortality of patients treated with ASPARLAS was 2.8% (3 out of 111); there were no induction deaths among 52 patients treated with pegaspargase.

Immunogenicity: Anti-Drug Antibody-Associated Adverse Reactions

In Study DFCI 11-001, hypersensitivity reactions occurred in 80% of ASPARLAS-treated patients with new or an increased titer of anti-drug antibodies (ADA) and in 6% of those without ADA [see Clinical Pharmacology (12.6)]. Two patients with ADA experienced anaphylaxis [see Warnings and Precautions (5.1)].

6.2 Postmarketing Experience

The following adverse reactions have been identified during post approval use of ASPARLAS. Because these reactions are reported voluntarily from a population of uncertain size, it is not always possible to reliably estimate their frequency or establish a causal relationship to drug exposure.

Hepatic: Veno-occlusive disease

8 USE IN SPECIFIC POPULATIONS

8.1 Pregnancy

Risk Summary

Based on published literature studies with L-asparaginase in pregnant animals, ASPARLAS can cause fetal harm when administered to a pregnant woman. There are no available data on ASPARLAS use in pregnant women to evaluate for a drug-associated risk of major birth defects, miscarriage, or adverse maternal or fetal outcomes. In animal reproduction studies, intravenous administration of calaspargase pegol-mknl to pregnant rats during organogenesis at doses 0.2 to 1 times the maximum recommended human doses did not result in adverse developmental outcomes. Published literature studies in pregnant rabbits, however, suggest asparagine depletion may cause harm to the animal offspring (see Data). Advise pregnant women of the potential risk to a fetus.

In the U.S. general population, the estimated background risk of major birth defects and miscarriage in clinically recognized pregnancies are 2 to 4% and 15 to 20%, respectively.

Data

Animal Data

In an embryo-fetal development study, calaspargase pegol-mknl was administered intravenously at doses of 75, 150, and 300 U/kg (0.2, 0.6 and 1 times the maximum recommended human dose, respectively, based on AUC) to pregnant rats during the period of organogenesis. Maternal toxicity of decreased body weight and food consumption was seen at all dose levels resulting in reductions in gravid uterine and placental weights, and slight reductions in fetal body weights. No evidence of structural abnormalities or embryo-fetal mortality were observed in this study at any of the doses tested. Published literature studies in which pregnant rabbits were administered L-asparaginase suggested harm to the animal offspring.

8.2 Lactation

Risk Summary

There are no data on the presence of calaspargase pegol-mknl in human milk, the effects on the breastfed child, or the effects on milk production. Because of the potential for adverse reactions in the breastfed child, advise women not to breastfeed during treatment with ASPARLAS and for 3 months after the last dose.

8.3 Females and Males of Reproductive Potential

ASPARLAS can cause fetal harm when administered to a pregnant woman [see Use in Specific Populations (8.1)].

Pregnancy Testing

Pregnancy testing is recommended in females of reproductive potential prior to initiating ASPARLAS.

Contraception

Advise females of reproductive potential to use effective non-hormonal contraceptive methods during treatment with ASPARLAS and for at least 3 months after the last dose.

8.4 Pediatric Use

The safety and effectiveness of ASPARLAS in the treatment of ALL have been established in pediatric patients 1 month to <17 years (no data for the age group <1 month old). Use of ASPARLAS in these age groups is supported by evidence from an adequate and well-controlled trial with additional safety from a second trial. The trials included 208 children with ALL or lymphoblastic lymphoma treated with ASPARLAS; there were 19 infants (1 month to <2 years old), 128 children (2 years to <12 years old), and 61 adolescents (12 years to <17 years old). There were no clinically meaningful differences in safety or nadir serum asparaginase activity across age groups [see Adverse Reactions (6.1), Clinical Studies (14)].

11 DESCRIPTION

Calaspargase pegol-mknl contains an asparagine specific enzyme derived from Escherichia coli, as a conjugate of L-asparaginase (L-asparagine amidohydrolase) and monomethoxypolyethylene glycol (mPEG) with a succinimidyl carbonate (SC) linker. The SC linker is a chemically stable carbamate bond between the mPEG moiety and the lysine groups of L-asparaginase.

L-asparaginase is a tetrameric enzyme that is produced endogenously by E. coli and consists of identical 34.5 kDa subunits. Approximately 31 to 39 molecules of SC-PEG are linked to L-asparaginase; the molecular weight of each SC-PEG molecule is about 5 kDa. The activity of ASPARLAS is expressed in units (U).

ASPARLAS injection is supplied as a clear, colorless, preservative-free, isotonic sterile solution in phosphate-buffered saline, pH 7.3 that requires dilution prior to intravenous infusion. Each vial of ASPARLAS contains 3,750 units in 5 mL of solution. Each milliliter contains 750 units of calaspargase pegol-mknl; dibasic sodium phosphate, USP (5.58 mg); monobasic sodium phosphate, USP (1.20 mg); and sodium chloride, USP (8.50 mg) in water for injection, USP.

12 CLINICAL PHARMACOLOGY

12.1 Mechanism of Action

L-asparaginase is an enzyme that catalyzes the conversion of the amino acid L-asparagine into aspartic acid and ammonia. The pharmacological effect of ASPARLAS is thought to be based on the killing of leukemic cells due to depletion of plasma asparagine. Leukemic cells with low expression of asparagine synthetase have a reduced ability to synthesize asparagine, and therefore depend on an exogenous source of asparagine for survival.

12.2 Pharmacodynamics

Calaspargase pegol-mknl pharmacodynamic (PD) response was assessed through measurement of plasma and cerebrospinal fluid (CSF) asparagine concentrations via an LC-MS/MS assay.

Asparagine concentrations in plasma (N=41) were maintained below the assay limit of quantification for more than 18 days following a single dose of ASPARLAS 2,500 U/m^2 during the induction phase. Mean CSF asparagine concentrations decreased from a pretreatment concentration of 0.8 µg/mL (N=10) to 0.2 µg/mL on Day 4 (N=37) and remained decreased at 0.2 µg/mL (N=35) 25 days after the administration of a single dose of ASPARLAS 2,500 U/m^2 in the induction phase.

12.3 Pharmacokinetics

Calaspargase pegol-mknl pharmacokinetics (PK) were assessed through measurement of plasma asparaginase activity via a coupled enzymatic assay.

The plasma asparaginase activity pharmacokinetics were characterized in 43 patients (1 to 26 years) with newly diagnosed high risk B-precursor ALL treated with a multidrug backbone therapy. Table 3 summarizes the plasma asparaginase activity pharmacokinetic parameters after a single dose of ASPARLAS 2,500 U/m^2 in the induction phase.

Table 3: Plasma Asparaginase Activity Pharmacokinetic Parameters After a Single Dose of ASPARLAS 2,500 U/m^2 in Patients with ALL in Study AALL07P4
Parameter | Arithmetic Mean (%CV) N=43
General
Cmax (U/mL) | 1.62 (23.0)
AUC0-25day (day∙U/mL) | 16.9 (23.2) [N=42 evaluable subjects.]
AUC0∞ (day∙U/mL) [Tmax generally near end of a 1 hour calaspargase pegol-mknl intravenous (IV) infusion.] | 25.5 (30.4)
Absorption
Tmax (h) | 1.17 (1.05, 5.47) [Median (10th, 90th percentiles).]
Distribution
Vss (L) | 2.96 (84.3)
Elimination
t1/2 (day) [Plasma asparaginase activity pharmacokinetics are nonlinear following ASPARLAS administration.] | 16.1 (51.9)
Clearance (L/day) | 0.147 (76.1)

12.6 Immunogenicity

As with all therapeutic proteins, there is a potential for immunogenicity. The detection of antibody formation is highly dependent on the sensitivity and specificity of the assay. Additionally, the observed incidence of antibody (including neutralizing antibody) positivity in an assay may be influenced by several factors, including assay methodology, sample handling, timing of sample collection, concomitant medications, and underlying disease. For these reasons, comparison of the incidence of antibodies to ASPARLAS in the studies described below with the incidence of antibodies in other studies or to other asparaginase products may be misleading.

Immunogenicity was assessed using enzyme linked immunosorbent assays (ELISA) in Study DFCI 11-001. Of 98 evaluable patients treated with ASPARLAS, 15 (15%) patients developed new or an increased titer of anti-drug antibodies (ADA) during treatment; 14 of these 15 patients were positive for anti-PEG antibodies. The presence of ADA correlated with the occurrence of hypersensitivity reactions [see Adverse Reactions (6.1)]. There is insufficient information to determine whether the development of antibodies is associated with altered pharmacokinetics (i.e., loss of asparaginase activity).

Specific Populations

The impact of renal and hepatic impairment on the PK of calaspargase pegol-mknl is unknown.

13 NONCLINICAL TOXICOLOGY

13.1 Carcinogenesis, Mutagenesis, Impairment of Fertility

Carcinogenicity, mutagenicity, and impairment of fertility studies have not been conducted with calaspargase pegol-mknl.

14 CLINICAL STUDIES

14.1 Acute Lymphoblastic Leukemia

The determination of efficacy was based on a demonstration of the achievement and maintenance of nadir serum asparaginase activity (NSAA) above the level of 0.1 U/mL using ASPARLAS 2500 U/m^2 intravenously every 3 weeks. The pharmacokinetics of ASPARLAS were studied when used in combination with multiagent chemotherapy in 124 patients with B-cell lineage acute lymphoblastic leukemia (ALL). Among these patients, the median age was 11.5 years (range, 1-26); 62 (50%) were male, 102 (82%) white, 6 (5%) Asian, 5 (4%) Black or African American, 2 (2%) Native Hawaiian or Pacific Islander and 9 (7%) other or unknown. The results showed that 123 (99%, 95% CI: 96%-100%) of the 124 patients maintained NSAA >0.1 U/mL at weeks 6, 12, 18, 24, and 30.

16 HOW SUPPLIED/STORAGE AND HANDLING

ASPARLAS (calaspargase pegol-mknl) injection is supplied as a clear, colorless, preservative-free sterile solution in a single-dose vial containing 3,750 units of calaspargase pegol-mknl per 5 mL solution (NDC 72694-515-01).

STORAGE AND HANDLING

Store ASPARLAS refrigerated at 2°C to 8°C (36°F to 46°F) in the original carton to protect from light. Do not shake or freeze product. Unopened vials may be stored at room temperature (15°C to 25°C [59°F to 77°F]) for no more than 48 hours.

17 PATIENT COUNSELING INFORMATION

Hypersensitivity

Inform patients on the possibility of serious allergic reactions, including anaphylaxis. Instruct the patient on the symptoms of allergic reactions and to seek medical advice immediately if they experience such symptoms [see Warnings and Precautions (5.1)].

Pancreatitis

Instruct patients on the signs and symptoms of pancreatitis and to seek immediate medical attention if they experience severe abdominal pain [see Warnings and Precautions (5.2)].

Instruct patients on the risk of hyperglycemia and glucose intolerance. Advise patients to seek medical advice if they experience excessive thirst or any increase in the volume or frequency of urination [see Dosage and Administration (2.3)].

Thrombosis

Instruct patients on the risk of thrombosis and to seek medical advice immediately if they experience severe headache, arm or leg swelling, shortness of breath, or chest pain [see Warnings and Precautions (5.3)].

Hemorrhage

Advise patients to report any unusual bleeding or bruising to their healthcare provider [see Warnings and Precautions (5.4)].

Hepatotoxicity , including Veno-Occlusive Liver Disease (VOD)

Inform patients that liver problems, including severe, life-threatening, or fatal VOD and abnormalities in liver tests, may develop during ASPARLAS treatment. Advise patients to contact their healthcare provider immediately if they experience jaundice, rapid weight gain, abdominal swelling, or right upper abdominal pain or tenderness [see Warnings and Precautions (5.5)].

Pregnancy

Advise pregnant women of the potential risk to a fetus. Advise females of reproductive potential to inform their healthcare provider of a known or suspected pregnancy [see Use in Specific Populations (8.1)].

Advise females of reproductive potential to use effective non-hormonal contraception during treatment with ASPARLAS and for 3 months after the last dose [see Use in Specific Populations (8.3)].

Lactation

Advise women not to breastfeed during treatment with ASPARLAS and for at least 3 months after the last dose [see Use in Specific Populations (8.2)].

Manufactured by:

Servier Pharmaceuticals LLC
Boston, MA 02210
U.S. License No. 2125

ASPARLAS is a registered trademark of Servier IP UK Ltd, a wholly owned, indirect subsidiary of Les Laboratoires Servier.

Servier and the Servier logo are trademarks of Les Laboratoires Servier.

I-008-21-US-E
ASP-005

PRINCIPAL DISPLAY PANEL - 5 mL Vial Carton

NDC 72694-515-01

ASPARLAS®
calaspargase
pegol-mknl

Injection

3750 units/5 mL
(750 units/mL)

For Intravenous Infusion
Only

One single-dose vial.
Discard unused portion.

Must dilute before use.

Rx ONLY

SERVIER